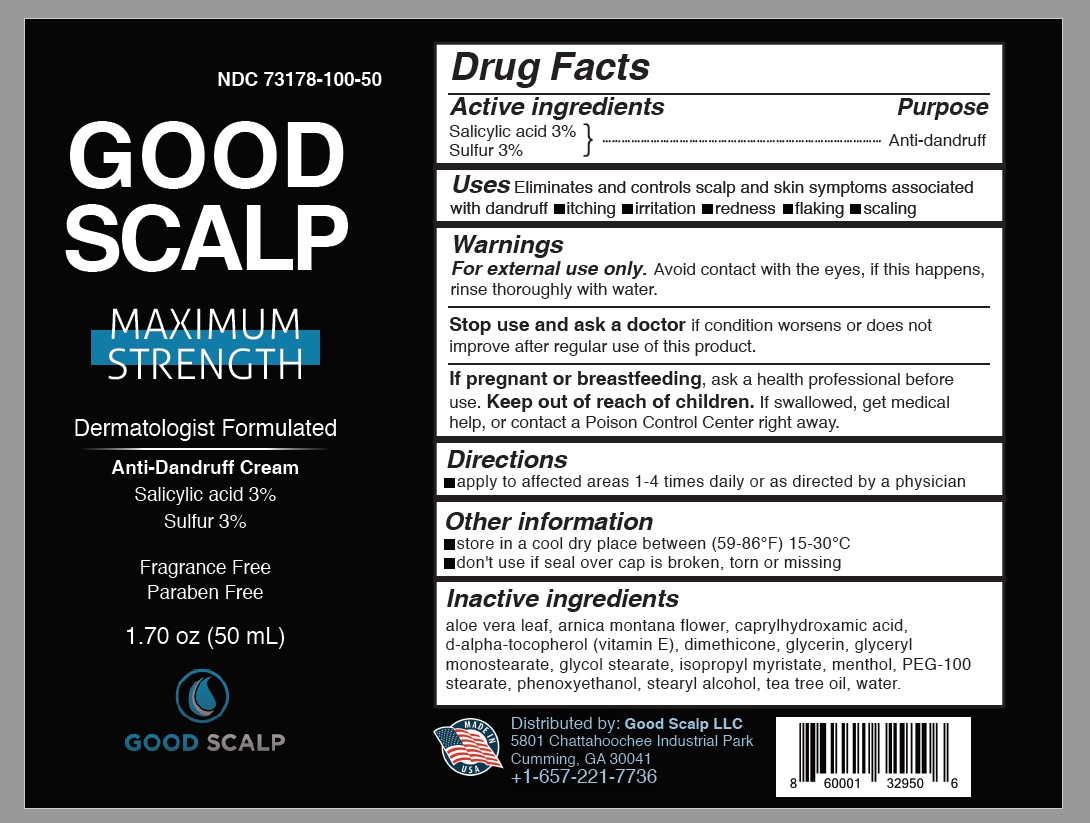 DRUG LABEL: Good Scalp
NDC: 73178-100 | Form: LOTION
Manufacturer: Good Scalp LLC
Category: otc | Type: HUMAN OTC DRUG LABEL
Date: 20190219

ACTIVE INGREDIENTS: SALICYLIC ACID 3 g/100 g; SULFUR 3 g/100 g
INACTIVE INGREDIENTS: GLYCERYL MONOSTEARATE; ISOPROPYL MYRISTATE; GLYCERIN; CAPRYLHYDROXAMIC ACID; GLYCOL STEARATE; STEARYL ALCOHOL; ARNICA MONTANA FLOWER; PHENOXYETHANOL; TEA TREE OIL; .ALPHA.-TOCOPHEROL, D-; WATER; MENTHOL; DIMETHICONE 1000; ALOE VERA LEAF; PEG-100 STEARATE

Good Scalp

Active Ingridients

Active ingredients | Purpose
Salicylic acid 3%..............................................; Sulfur 3%......................................................... | Anti-dandruff

Use

Eliminates and controls scalp and skin symptoms associated with dandruff

- itching
- irritation
- redness
- flaking
- scaling

Warning

For external use only. Avoid contact with the eyes, if this happens,
rinse thoroughly with water.

Stop use and ask a doctor if

condition worsens or does not improve after regular use of this product.

If pregnant or breastfeeding

ask a health professional before use.

Keep out of reach of children.

If swallowed, get medical help, or contact a Poison Control Center right away.

Directions

- apply to affected areas 1-4 times daily or as directed by a physician

Other information

- store in a cool dry place between (59-86°F) 15-30°C
- don't use if seal over cap is broken, torn or missing

Inactive ingredients

aloe vera leaf, arnica montana flower, caprylhydroxamic acid,
d-alpha-tocopherol (vitamin E), dimethicone, glycerin, glyceryl
monostearate, glycol stearate, isopropyl myristate, menthol, PEG-100
stearate, phenoxyethanol, stearyl alcohol, tea tree oil, water.

Questions & Comments

Distributed by: Good Scalp LLC
5801 Chattahoochee Industrial Park
Cumming, GA 30041
+1-657-221-7736

Principal Display Panel

GOOD
SCALP

MAXIMUM
STRENGTH

Dermatologist Formulated

Anti-Dandruff Cream
Salicylic acid 3%
Sulfur 3%

Fragrance Free

Paraben Free

1.70 oz (50 mL)

GOOD SCALP